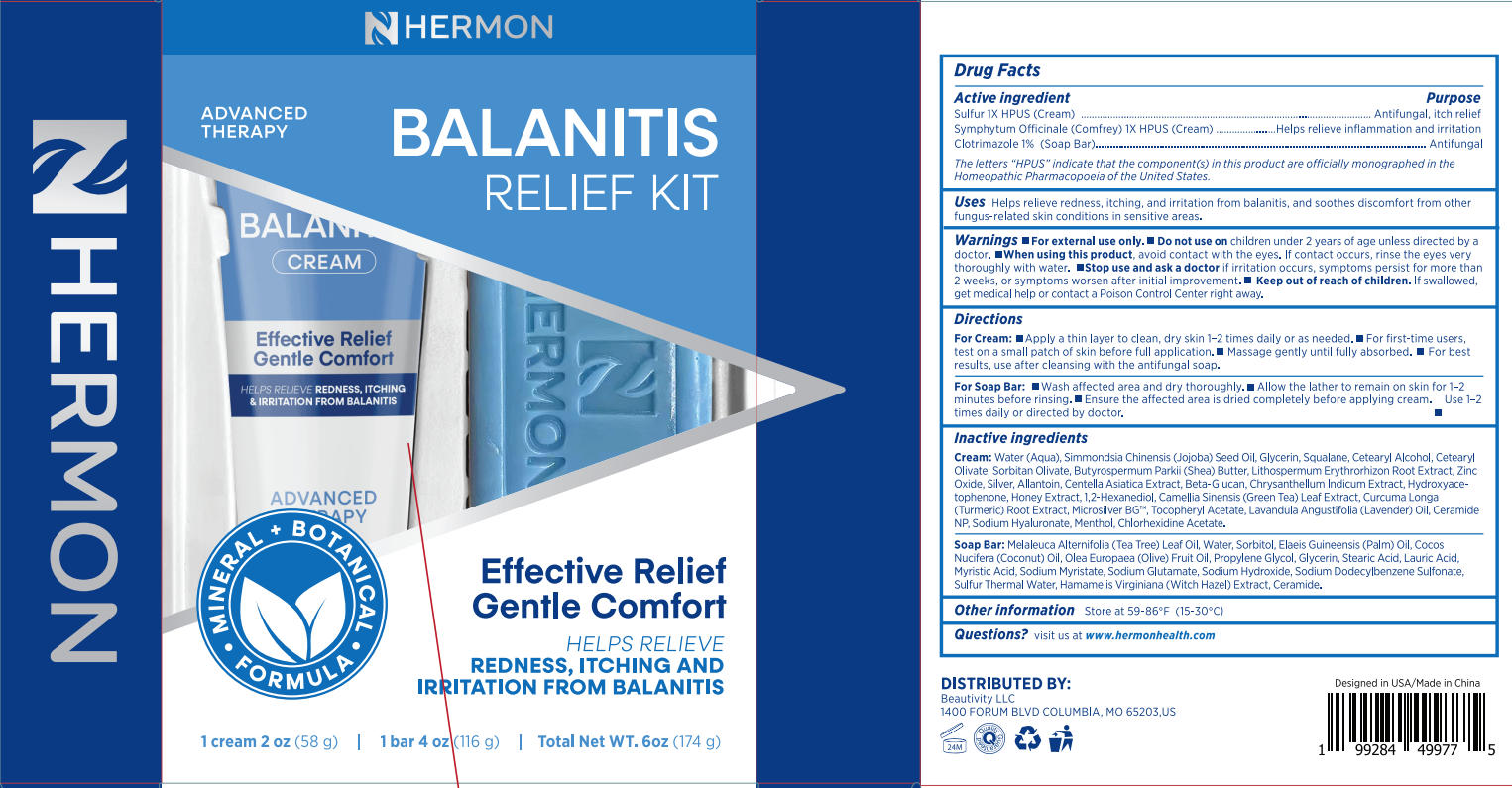 DRUG LABEL: Hermon Balanitis relief kit
NDC: 85398-014 | Form: KIT | Route: TOPICAL
Manufacturer: Beautivity LLC
Category: otc | Type: HUMAN OTC DRUG LABEL
Date: 20250902

ACTIVE INGREDIENTS: CLOTRIMAZOLE 1.16 g/116 g; SYMPHYTUM OFFICINALE WHOLE 1 [hp_X]/58 g; SULFUR 1 [hp_X]/58 g
INACTIVE INGREDIENTS: LAURIC ACID; MYRISTIC ACID; CERAMIDE 1; OLEA EUROPAEA (OLIVE) FRUIT OIL; MELALEUCA ALTERNIFOLIA (TEA TREE) LEAF OIL; GLYCERIN; COCOS NUCIFERA (COCONUT) OIL; ELAEIS GUINEENSIS (PALM) OIL; STEARIC ACID; SODIUM DODECYLBENZENESULFONATE; SODIUM MYRISTATE; WATER; SORBITOL; SODIUM HYDROXIDE; PROPYLENE GLYCOL; SODIUM GLUTAMATE; HAMAMELIS VIRGINIANA (WITCH HAZEL) LEAF WATER; SORBITAN OLIVATE; ALPHA-TOCOPHEROL ACETATE; TRANSFORMING GROWTH FACTOR BETA RECEPTOR TYPE 3; CURCUMA LONGA (TURMERIC) ROOT; CETEARYL ALCOHOL; SODIUM HYALURONATE; CHLORHEXIDINE ACETATE; CAMELLIA SINENSIS LEAF; GLYCERIN; SILVER; BUTYROSPERMUM PARKII (SHEA) BUTTER; SQUALANE; SIMMONDSIA CHINENSIS (JOJOBA) SEED OIL; ZINC OXIDE; 1,2-HEXANEDIOL; MENTHOL; HONEY; LAVANDULA ANGUSTIFOLIA (LAVENDER) OIL; WATER; CETEARYL OLIVATE; LITHOSPERMUM ERYTHRORHIZON ROOT; CERAMIDE NP; ALLANTOIN; CENTELLA ASIATICA TRITERPENOIDS; SILVER PARTICLE (10 MICRON); CHRYSANTHELLUM INDICUM TOP; HYDROXYACETOPHENONE

Initial Drug Listing - Hermon Balanitis relief kit

ACTIVE INGREDIENT

- Sulfur 1X HPUS (cream)
- Symphytum Officinale (Comfrey) 1X HPUS (Cream)
- Clotrimazole 1%(Soap Bar)

PURPOSE

- Antifungal, itch relief.
- Helps relieve inflammation and irritation
- Antifungal

DOSAGE AND ADMINISTRATION

Helps relieve redness, itching, and irritation from balanitis, and soothes discomfort from other
fungus-related skin conditions in sensitive areas.

WARNINGS

For external use only

DO NOT USE

children under 2 years of age unless directed by adoctor.

WHEN USING

avoid contact with the eyes. if contact occurs, rinse the eyes very thoroughly with water.

ASK DOCTOR

if irritation occurs, symptoms persist for more than 2 weeks, or symptoms worsen after initial improvement

KEEP OUT OF REACH OF CHILDREN

lf swallowed,get medical help or contact a Poison Control Center right away.

INDICATIONS AND USAGE

For Cream:

- Apply a thin layer to clean, dry skin 1-2 times daily or as needed.
- For first-time users,test on a small patch of skin before full application.
- Massage gently until fully absorbed.
- For bestresults, use after cleansing with the antifungal soap.

For Soap Bar:

- Wash affected area and dry thoroughly.
- Allow the lather to remain on skin for 1-2minutes before rinsing.
- Ensure the affected area is dried completely before applying cream.
- Use 1-2times daily or directed by doctor.

INACTIVE INGREDIENT

Cream: Water (Aqua), Simmondsia chinensis (Jojoba) Seed Oil, Glycerin, Squalane, Cetearyl Alcohol, Cetearyl Olivate, Sorbitan Olivate, Butyrospermum Parki (Shea) Butter, Lithospermum Erythrorhizon Root Extract, ZincOxide, Silver, Allantoin, Centella Asiatica Extract, Beta-Glucan, Chrysanthellum indicum Extract, Hydroxyace-tophenone, Honey Extract, 1,2-Hexanediol, Camellia Sinensis (Green Tea) Leaf Extract, Curcuma Longa(Turmeric) Root Extract, Microsilver BG", Tocopheryl Acetate, Lavandula Angustifolla (Lavender) Oil, CeramideNP, Sodium Hyaluronate, Menthol, Chlorhexidine Acetate.

Soap Bar: Melaleuca Alternifolia (Tea Tree) Leaf Oil, Water, Sorbitol, Elaeis Guineensis (Palm) Oil, Cocos Nucifera (Coconut) Oil, Olea Europaea (Olive) Fruit Oil, Propylene Glvcol, Glycerin, Stearic Acid, Lauric Acid. Myristic Acid, Sodium Myristate, Sodium Glutamate, Sodium Hydroxide, Sodium Dodecylbenzene Sulfonate,Sulfur Thermal Water, Hamamelis Virginiana (Witch Hazel) Extract, Ceramide.

OTHER SAFETY INFORMATION

store at 59-86°F(15-30°C)

QUESTIONS

visit us at www.hermonhealth.com